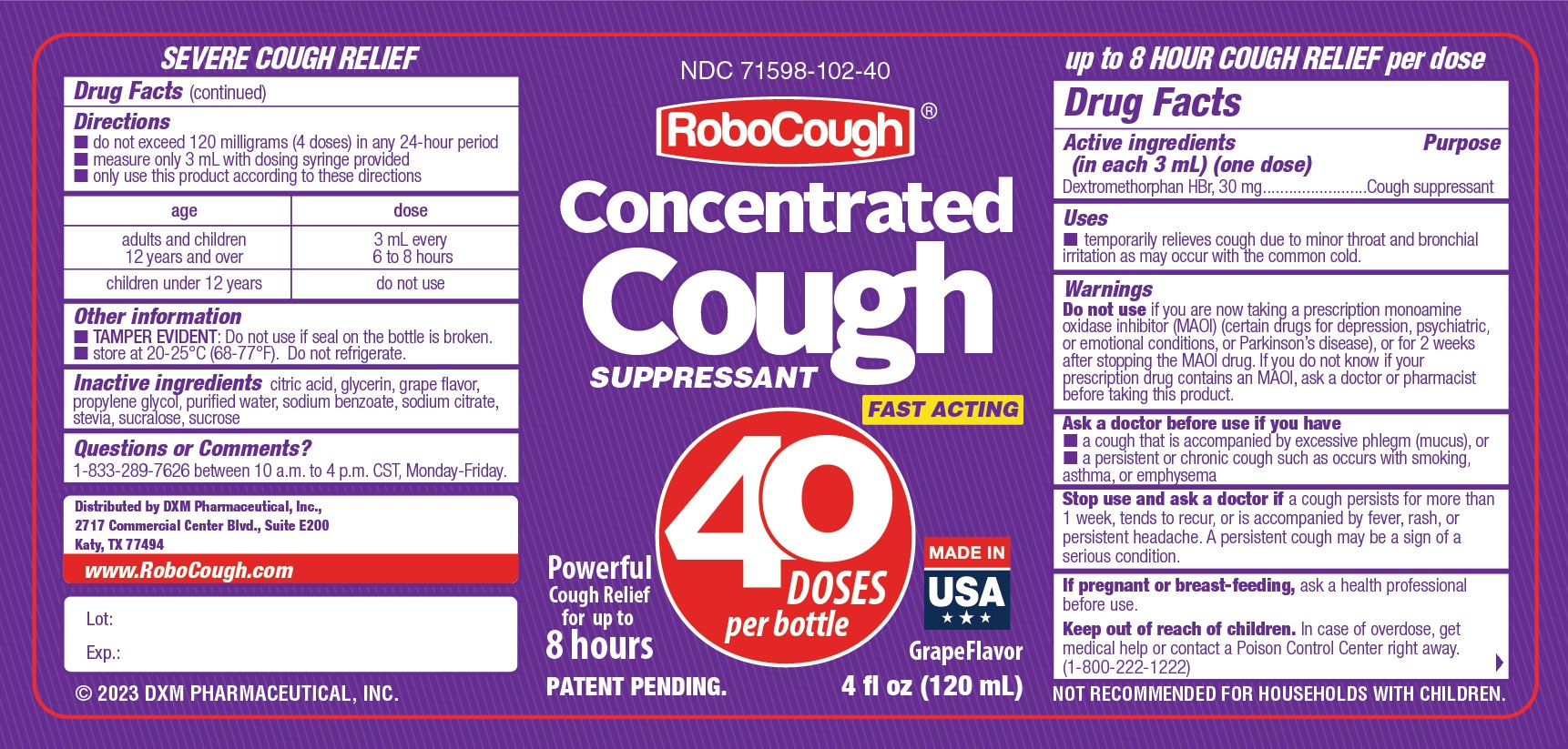 DRUG LABEL: RoboCough
NDC: 71598-102 | Form: LIQUID
Manufacturer: DXM Pharmacuetical, Inc.
Category: otc | Type: HUMAN OTC DRUG LABEL
Date: 20250110

ACTIVE INGREDIENTS: DEXTROMETHORPHAN HYDROBROMIDE 30 mg/3 mL
INACTIVE INGREDIENTS: ANHYDROUS CITRIC ACID; GLYCERIN; PROPYLENE GLYCOL; WATER; SODIUM BENZOATE; SODIUM CITRATE; STEVIA LEAF; SUCRALOSE; SUCROSE

Active ingredient

(in each 3 mL) (one dose) Dextromethrophan HBr, 30 mg

Purpose

Cough suppressant

Uses

- Temporarily relieves cough due to minor throat and bronchial irritation as may occur with the common cold.

Warning

Do not useif you are now taking a prescription monoamine oxidase inhibitor (MAOI) (certain drugs for depression, psychiatric, or emotional conditions, or Parkinson's disease), or for 2 weeks after stopping the MAOI drug. If you do not know if your prescription drug contains an MAOI, ask a doctor or pharmacist before taking this product.

Ask a doctor before use if you have
• a cough that is accompanied by excessive phlegm (mucus), or
• a persistent or chronic cough such as occurs with smoking, asthma, or emphysema.

Stop use and ask a doctor ifa cough persists for more than 1 week, tends to recur, or is accompanied by fever, rash, or persistent headache. A persistent cough may be a sign of a serious condition.

If pregnant or breast-feeding, ask a health professional before use.

Keep out of reach of children. In case of overdose, get medical help or contact a Poison Control Center right away. (1-800-222-1222)

Directions
• do not exceed 120 milligrams (4 doses) in any 24-hour period
• measure only 3 mL with dosing syringe provided
• only use this product according to these directions

age dose

adults and children 12 years and over

3mL every 6 to 8 hours

children under 12 years

do not use

Other information

• TAMPER EVIDENT: Do not use if seal on the bottle is broken.
• store at 20-25°C (68-77°F). Do not refrigerate.

Inactive ingredients

Citric acid, glycerin, grape flavor, propylene glycol, purified water, sodium benzoate, sodium citrate, stevia, sucralose, sucrose

Questions or comments?

833-289-7626 between 10 a.m. to 4 p.m. CST, Monday-Friday